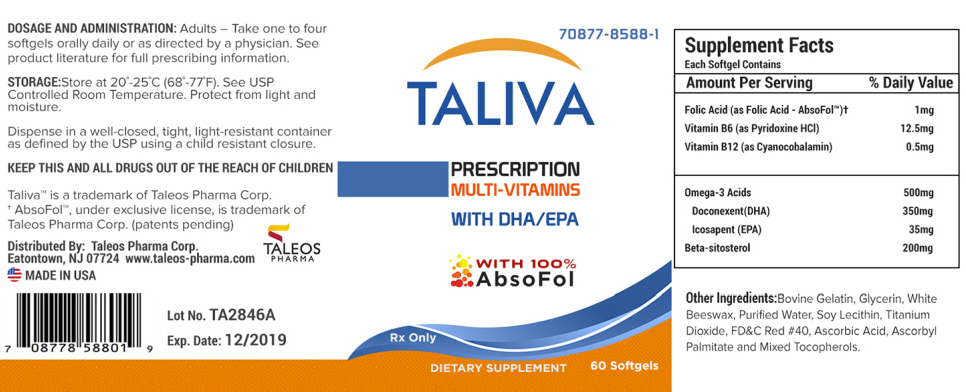 DRUG LABEL: TALIVA
NDC: 70877-8588 | Form: CAPSULE, GELATIN COATED
Manufacturer: Taleos Pharma
Category: other | Type: DIETARY SUPPLEMENT
Date: 20180105

ACTIVE INGREDIENTS: Folic Acid 1 mg/1 1; Pyridoxine Hydrochloride 12.5 mg/1 1; Cyanocobalamin 0.5 mg/1 1; Doconexent 350 mg/1 1; Icosapent 35 mg/1 1; Omega-3 Fatty Acids 35 mg/1 1; .Beta.-Sitosterol 200 mg/1 1
INACTIVE INGREDIENTS: Gelatin, Unspecified; Glycerin; White Wax; Water; Lecithin, Soybean; Titanium Dioxide; FD&C Red NO. 40; Ascorbic Acid; Ascorbyl Palmitate; Tocopherol

TALIVA Softgels

HEALTH CLAIM

Rx Only

DESCRIPTION

TALIVA is a prescription multi-vitamin in the form of a red, opaque softgel.

INDICATION AND USAGE

TALIVA is a prescription multi-vitamin supplement with DHA and EPA that can be taken to improve nutritional status in conditions requiring Essential Fatty Acid, Vitamin B12 and B6 and Folic Acid supplementation capsule.

CONTRAINDICATIONS

This product is contraindicated in patients with a known hypersensitivity to any of the ingredients.

WARNING

Folic Acid in doses above 0.1 mg daily may obscure pernicious anemia in that hematological remission can occur while neurological manifestations remain progressive. Folic Acid alone is improper therapy in the treatment of pernicious anemia and other megaloblastic anemias where vitamin B12 is deficient.

Ingestion of more than 3 grams of omega-3 fatty acids per day has been shown to have potential antithrombotic effects, including increased bleeding time and INR. Administration of omega-3 fatty acids should be avoided in patients on anticoagulants and in those known to have an inherited or acquired bleeding diathesis.

KEEP THIS AND ALL MEDICATIONS OUT OF THE REACH OF CHILDREN.

PRECAUTIONS

Folic Acid in doses above 0.1 mg daily may obscure pernicious anemia in that hematological remission can occur while neurological manifestations remain progressive.

ADVERSE REACTIONS

Allergic sensitization has been reported following both oral and parenteral administration of folic acid.

DOSAGE AND ADMINISTRATION

Adults

One to four softgels orally daily or as directed by a physician.

Supplement Facts
Serving Size: 1 Softgel | Servings per Container: 60
Amount Per Serving
Folic Acid (as Folic Acid - AbsoFol™) [AbsoFol™, under exclusive license, is trademark of Taleos Pharma Corp. (patents pending)] |  | 1mg
Vitamin B6 (as Pyridoxine HCl) |  | 12.5mg
Vitamin B12 (as Cyanocobalamin) |  | 0.5mg
Omega-3 Acids |  | 500mg
Doconexent (DHA) |  | 350mg
Icosapent (EPA) |  | 35mg
Beta-sitosterol |  | 200mg

STORAGE

Store at 20° - 25°C (68° - 77°F); excursions permitted to 15° - 30°C (59° - 86°F) [See USP Controlled Room Temperature.]

Dispense in a well-closed, tight, light-resistant container as defined by the USP using a child resistant closure.

HOW SUPPLIED

TALIVA softgels are supplied as red, opaque, oblong, coated softgels. TALIVA softgels are available in bottles of 60 (NDC: 70877-8588-01).

HEALTH CLAIM

Distributed By:
Taleos Pharma Corp.
Eatontown, NJ 07724
www.taleos-pharma.com

TALIVA, ABSOFOL and TALEOS are trademarks of Taleos Pharma Corp.

PRINCIPAL DISPLAY PANEL - 60 Softgel Bottle Label

70877-8588-1

TALIVA

PRESCRIPTION
MULTI-VITAMINS

WITH DHA/EPA

WITH 100%
AbsoFol

Rx Only

DIETARY SUPPLEMENT
60 Softgels